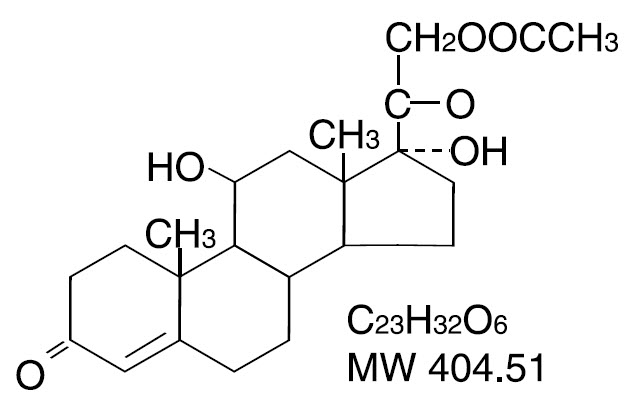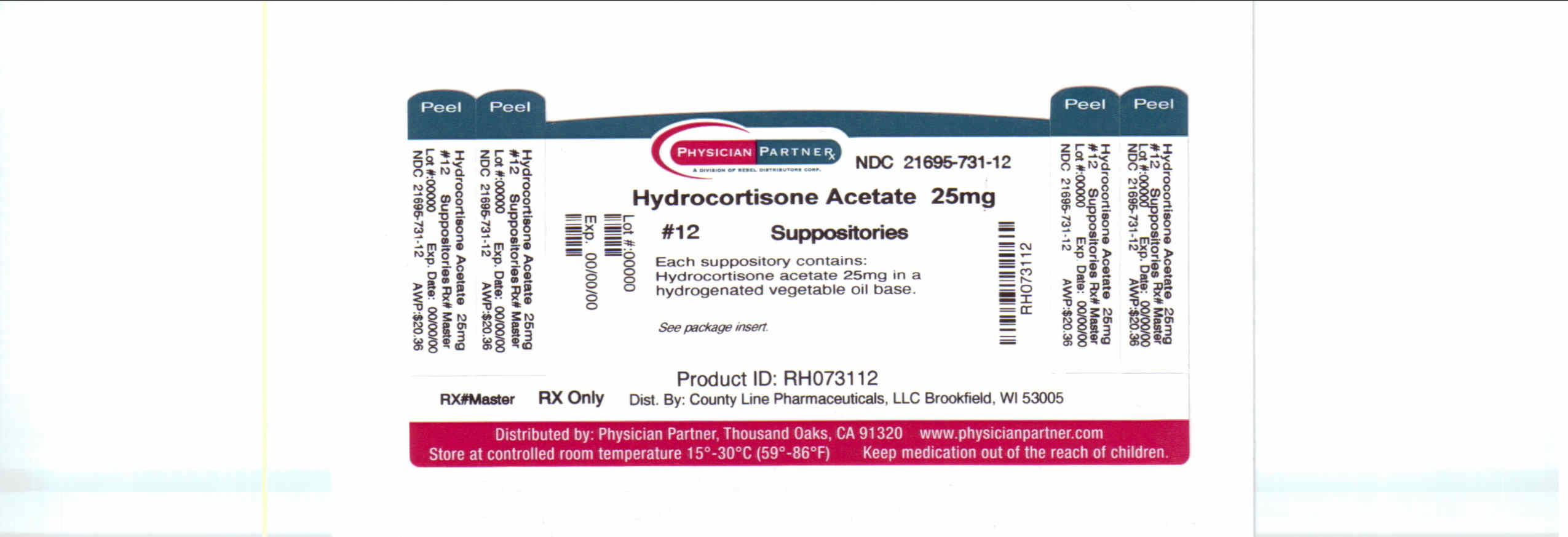 DRUG LABEL: Hydrocortisone Acetate
NDC: 21695-731 | Form: SUPPOSITORY
Manufacturer: Rebel Distributors Corp
Category: prescription | Type: HUMAN PRESCRIPTION DRUG LABEL
Date: 20110608

ACTIVE INGREDIENTS: HYDROCORTISONE ACETATE 30 mg/1 1
INACTIVE INGREDIENTS: HYDROGENATED PALM OIL; COLLOIDAL SILICON DIOXIDE; BUTYLATED HYDROXYANISOLE

Hydrocortisone Acetate

PROCTOCORT®

Hydrocortisone Acetate

Rectal Suppositories, 25 mg

DESCRIPTION

Each Hydrocortisone Acetate 25 mg Suppository contains 25 mg hydrocortisone acetate in a hydrogenated vegetable oil base. Hydrocortisone acetate is a corticosteroid. Chemically, hydrocortisone acetate is a pregn-4-ene-3, 20-dione, 21-(acetyloxy)-11, 17-dihydroxy-(11β) with the following structural formula:

CLINICAL PHARMACOLOGY

In normal subjects, about 26% of hydrocortisone acetate is absorbed when the suppository is applied to the rectum. Absorption of hydrocortisone acetate may vary across abraded or inflamed surfaces.

Topical steroids are primarily effective because of their anti-inflammatory, anti-pruritic and vasoconstrictive action.

INDICATIONS AND USAGE

For use in inflamed hemorrhoids, postirradiation (factitial) proctitis; as an adjunct in the treatment of chronic ulcerative colitis; cryptitis; and other inflammatory conditions of anorectum and pruritus ani.

CONTRAINDICATIONS

Hydrocortisone Acetate Suppositories are contraindicated in those patients having a history of hypersensitivity to any of the components.

PRECAUTIONS

Do not use unless adequate proctologic examination is made.

If irritation develops, the product should be discontinued and appropriate therapy instituted.

In the presence of an infection, the use of an appropriate antifungal or antibacterial agent should be instituted. If a favorable response does not occur promptly, the hydrocortisone acetate should be discontinued until the infection has been adequately controlled.

Carcinogenesis: No long term studies in animals have been performed to evaluate the carcinogenic potential of corticosteroid suppositories.

Pregnancy Category C: In laboratory animals, topical steroids have been associated with an increase in the incidence of fetal abnormalities when gestating females have been exposed to rather low dosage levels. There are no adequate and well controlled studies in pregnant women. Hydrocortisone Acetate Suppositories should only be used during pregnancy if the potential benefit justifies the risk to the fetus. Drugs of this class should not be used extensively on pregnant patients, in large amounts, or for prolonged periods of time.

It is not known whether this drug is excreted in human milk and because many drugs are excreted in human milk and because of the potential for serious adverse reactions in nursing infants from Hydrocortisone Acetate Suppositories, a decision should be made whether to discontinue nursing or to discontinue the drug, taking into account the importance of the drug to the mother.

ADVERSE REACTIONS

The following local adverse reactions have been reported with hydrocortisone acetate suppositories; burning, itching, irritation, dryness, folliculitis, hypopigmentation, allergic contact dermatitis, secondary infection.

Drug abuse and dependence have not been reported in patients treated with hydrocortisone acetate suppositories.

OVERDOSAGE

If signs and symptoms of systemic overdosage occur, discontinue use.

DOSAGE AND ADMINISTRATION

For rectal administration. Detach one suppository from strip of suppositories. Remove the wrapper. Avoid excessive handling of the suppository which is designed to melt at body temperature. Insert suppository into the rectum with gentle pressure, pointed end first. Insert one suppository in the rectum twice daily, morning and night for two weeks, in nonspecific proctitis. In more severe cases, one suppository three times a day or two suppositories twice daily. In factitial proctitis, the recommended duration of therapy is six to eight weeks or less, according to the response of the individual case.

HOW SUPPLIED

Box of 12 suppositories - NDC 21695-731-12

Rx only.

Store at 20°–25°C (68°–77°F). See USP Controlled Room Temperature. Store away from heat. Protect from freezing.

For Inquiries call: 1-866-207-5636

Distributed by:

County Line Pharmaceuticals, LLC

Brookfield, WI 53005

Repackaged by:

Rebel Distributors Corp

Thousand Oaks, CA 91320